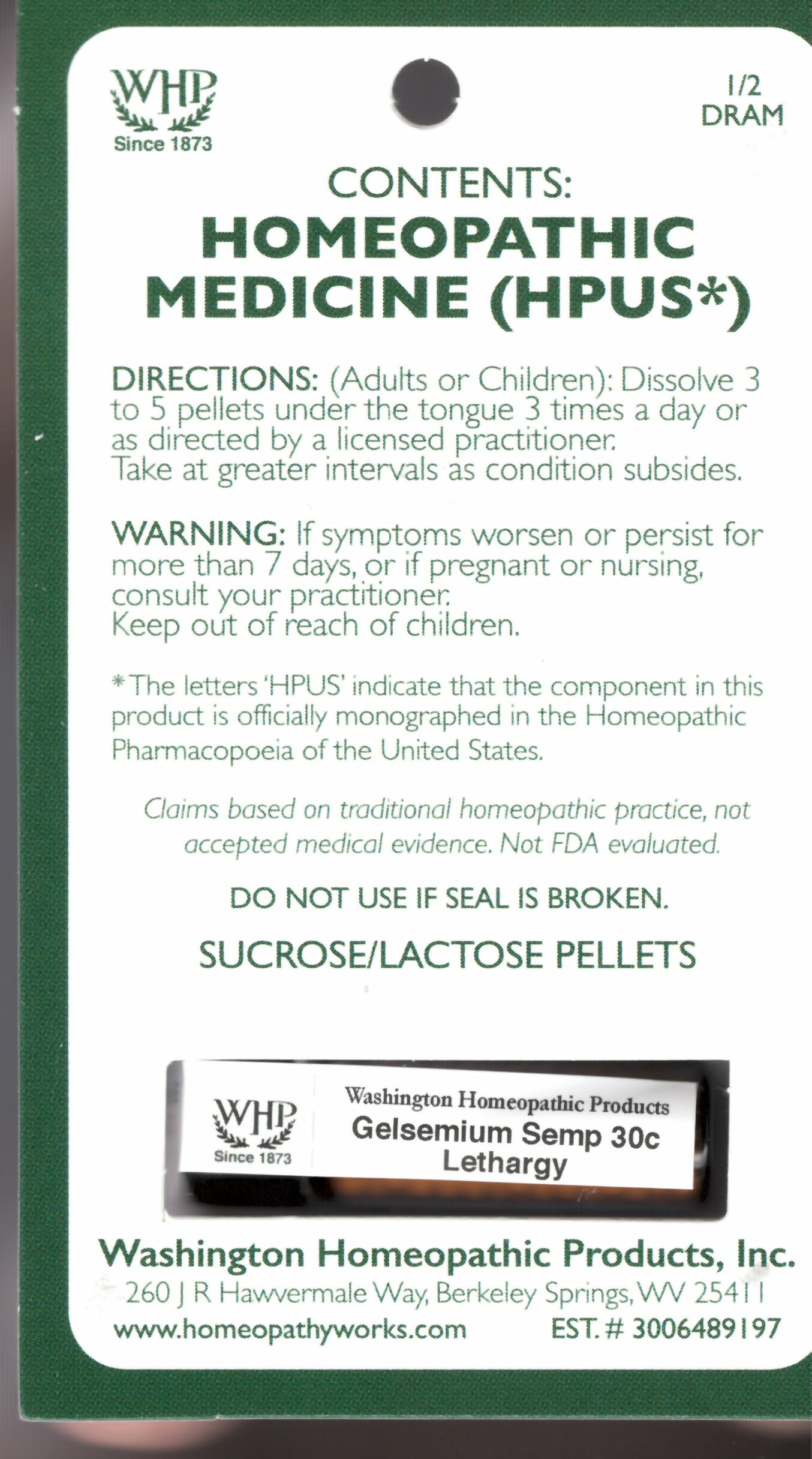 DRUG LABEL: Gelsemium Semp Kit Refill
NDC: 68428-099 | Form: PELLET
Manufacturer: Washington Homeopathic Products
Category: homeopathic | Type: HUMAN OTC DRUG LABEL
Date: 20231107

ACTIVE INGREDIENTS: GELSEMIUM SEMPERVIRENS ROOT 30 [hp_C]/1 1
INACTIVE INGREDIENTS: SUCROSE; LACTOSE

DRUG FACTS

ACTIVE INGREDIENTS

GELSEMIUM SEMPERVIRENS 30C

USES

To relieve the symptoms of lethargy.

KEEP OUT OF REACH OF CHILDREN

Keep this and all medicines out of reach of children.

INDICATIONS

GELSEMIUM SEMPERVIRENS Lethargy

STOP USE AND ASK DOCTOR

If symptoms persist/worsen or if pregnant/nursing, stop use and consult your practitioner.

DIRECTIONS

Adults: Dissolve 3 to 5 under the tongue three times a day or as directed by Lic. Practitioner. Take at greater intervals as condition subsides.

Children: Dissolve 3 to 5 under the tongue three times a day or as directed by Lic. Practitioner. Take at greater intervals as condition subsides.

INACTIVE INGREDIENTS

Sucrose/Lactose